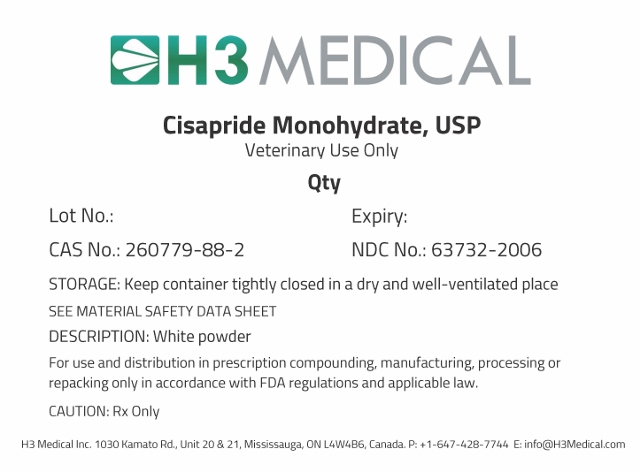 DRUG LABEL: Cisapride Monohydrate
NDC: 63732-2006 | Form: POWDER
Manufacturer: H3 Medical Inc.
Category: other | Type: BULK INGREDIENT
Date: 20190116

ACTIVE INGREDIENTS: CISAPRIDE MONOHYDRATE 1 g/1 g

Cisapride Monohydrate